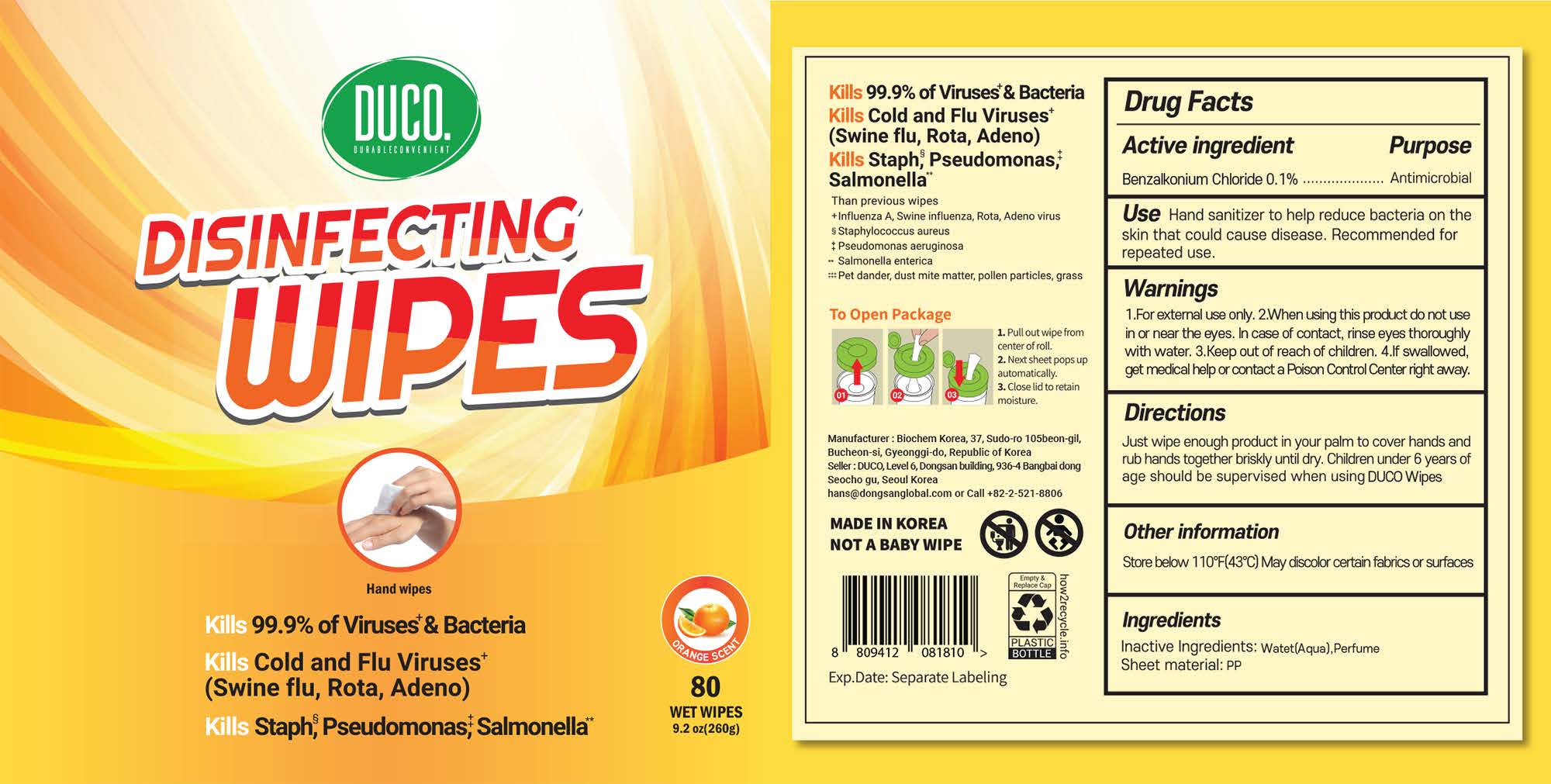 DRUG LABEL: DUCO
NDC: 74085-0012 | Form: LIQUID
Manufacturer: BIOCHEM KOREA CO., LTD
Category: otc | Type: HUMAN OTC DRUG LABEL
Date: 20210127

ACTIVE INGREDIENTS: BENZALKONIUM CHLORIDE 0.1 g/100 g
INACTIVE INGREDIENTS: WATER

ACTIVE INGREDIENT

BENZALKONIUM CHLORIDE 0.1%

INACTIVE INGREDIENT

PERFUME 0.1%

WATER 99.8%

KEEP OUT OF CHILDREN

WARNING

External use only

When using this product, do not use it in or near the eyes. In case of contact, rinse eyes thoroughly with water.

ASK DOCTOR

Stop use and ask a doctor if irritation or rash occurs.

If swallowed, get medical help or contact poison control center right away.

DO NOT USE

When using this product, do not use in or near the eyes. In case of contact, rinse eyes thoroughly with water

Stop use if irritation or rash occurs.

DIRECTION

Thoroughly wipe hands with the wipe.

Discard properly. Not flushable.

Be sure to close the lid to keep wipes moist.

INDICATIONS & USAGE

Use hand sanitizer to help reduce bacteria on the skin that could cause disease. Recommended for repeated use.

PURPOSE

Antiseptic hand-cleaning to reduce germs on hands.